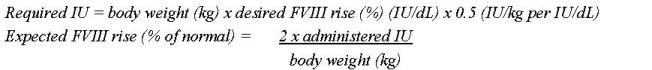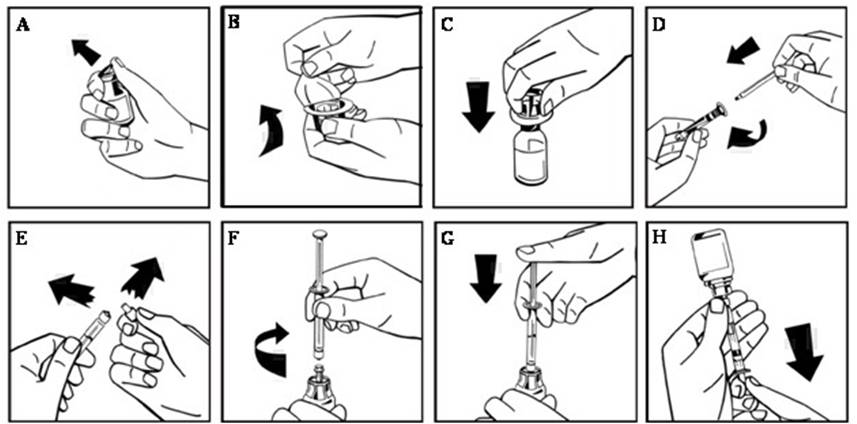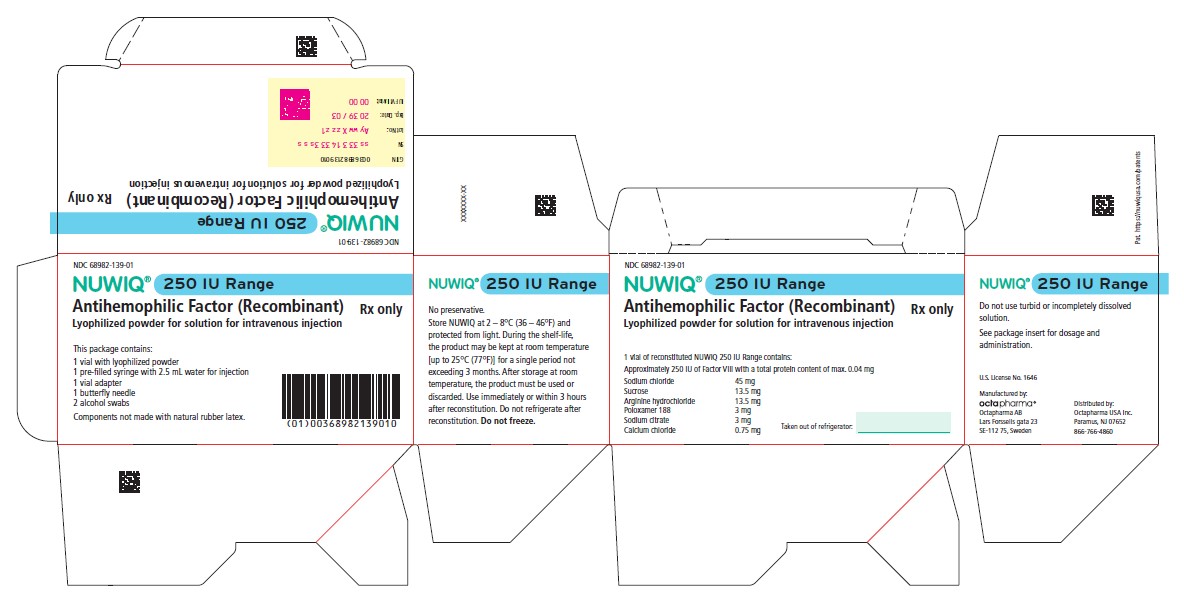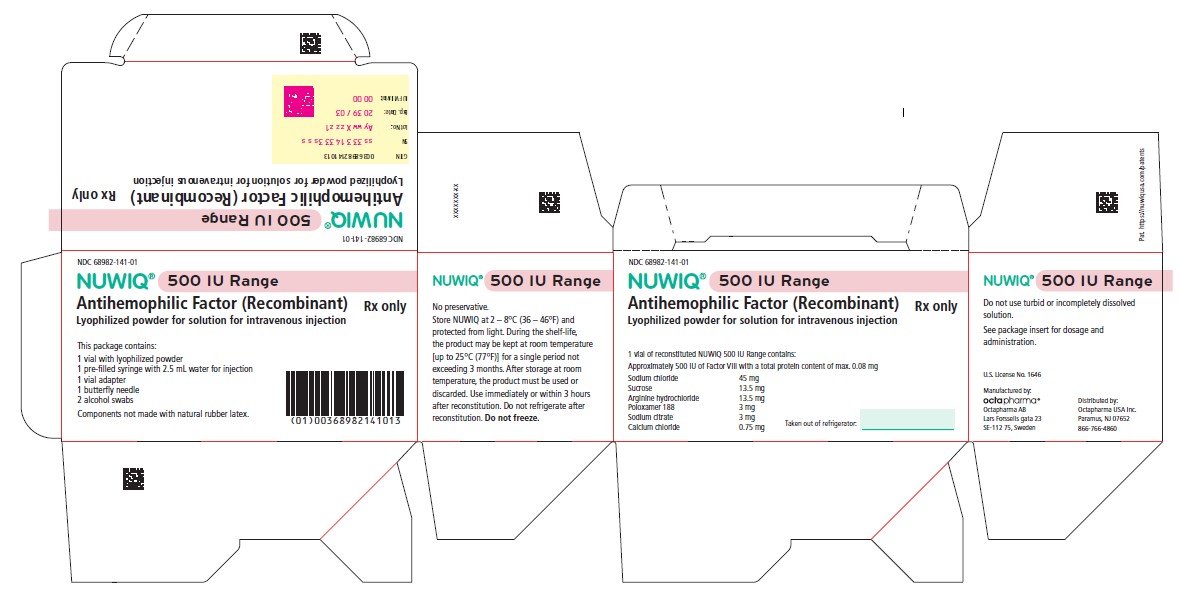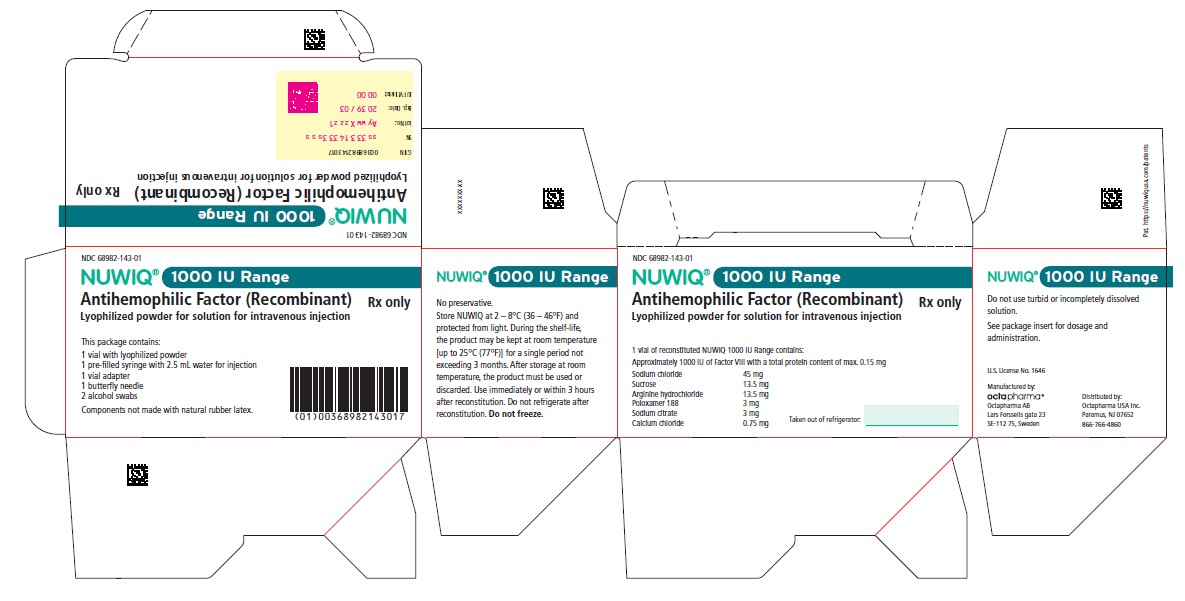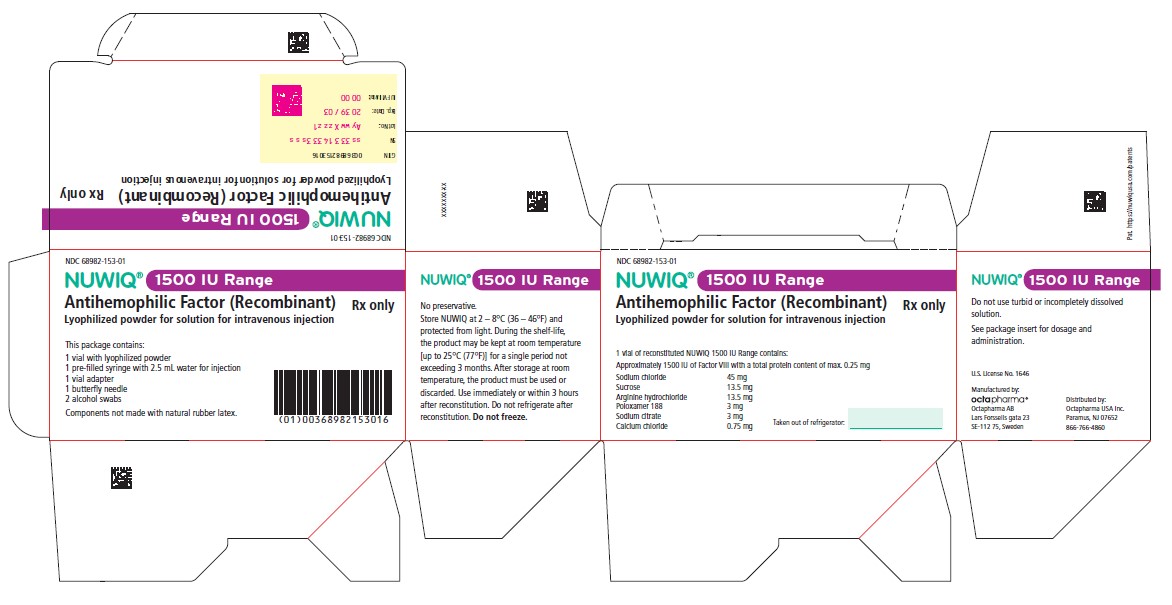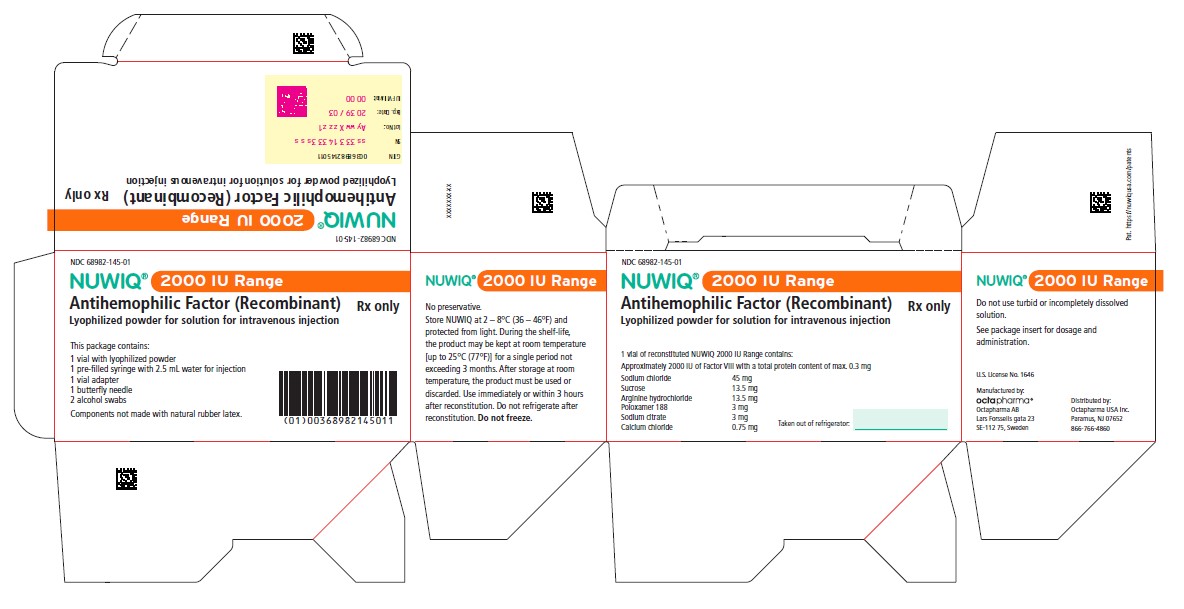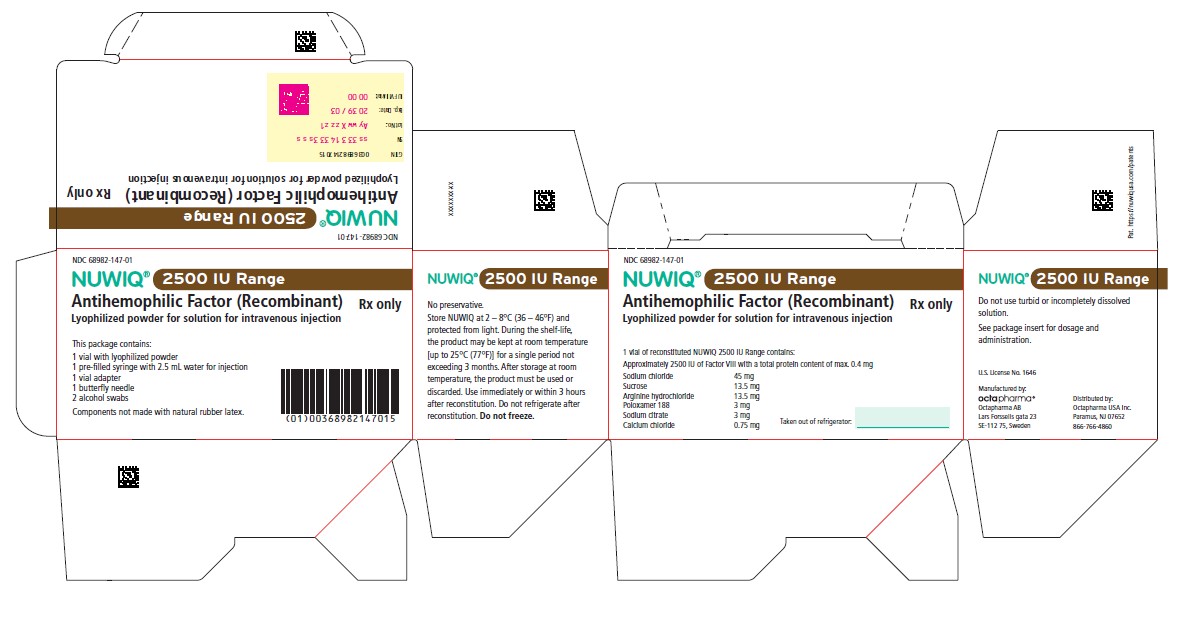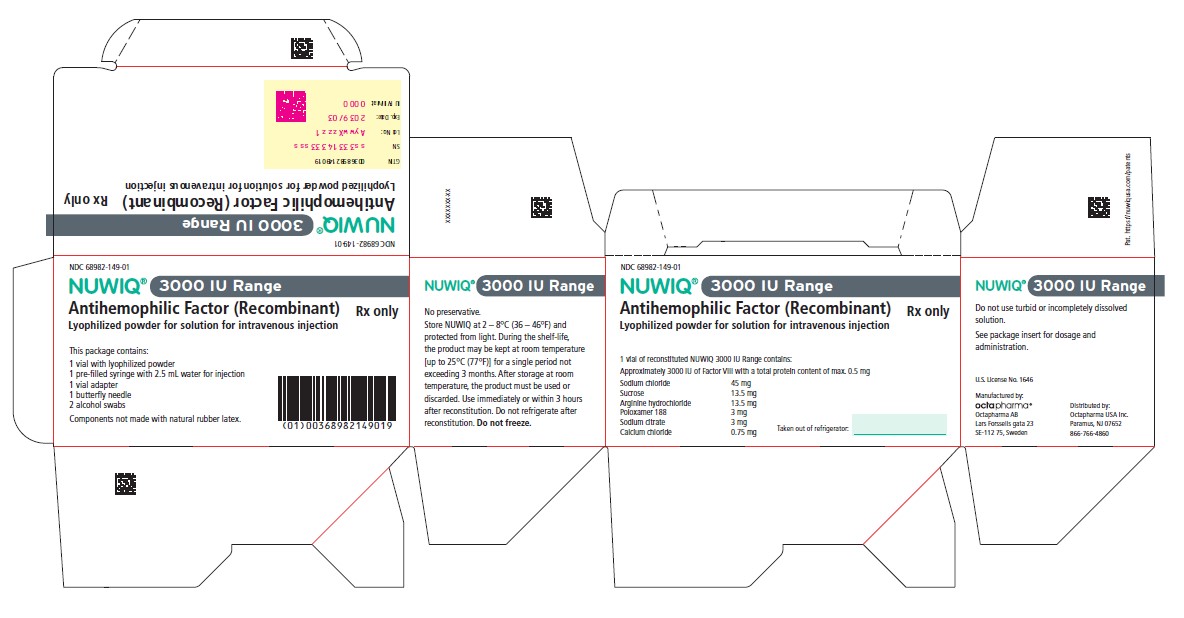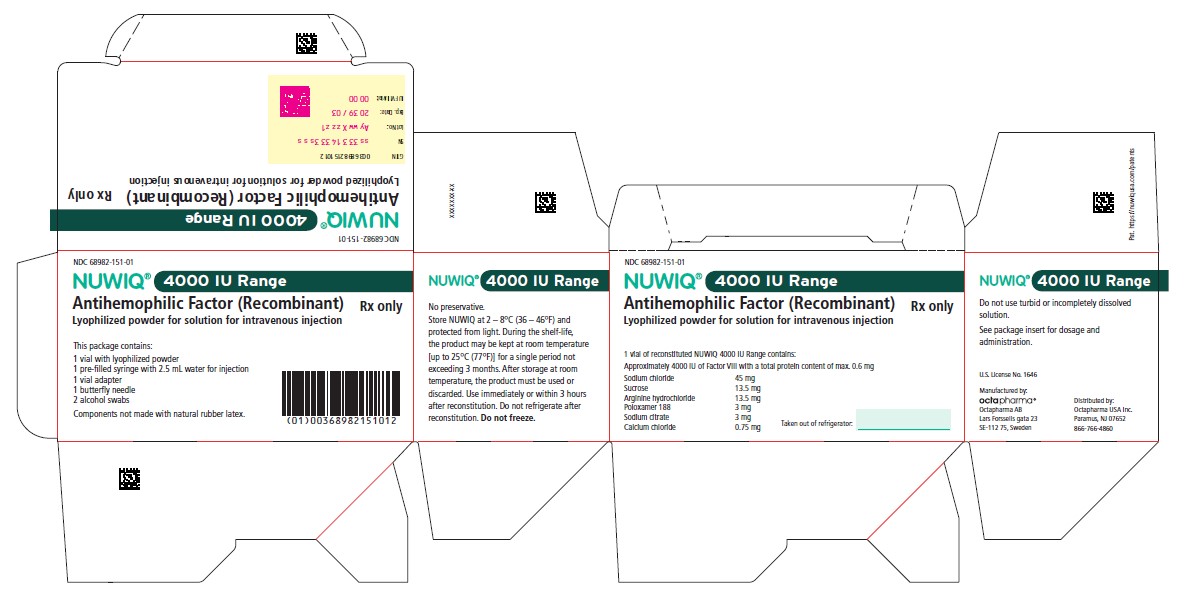 DRUG LABEL: NUWIQ
NDC: 68982-151 | Form: KIT | Route: INTRAVENOUS
Manufacturer: Octapharma USA Inc
Category: other | Type: PLASMA DERIVATIVE
Date: 20241226

ACTIVE INGREDIENTS: Simoctocog Alfa 4000 [iU]/2.5 mL

HIGHLIGHTS OF PRESCRIBING INFORMATION

These highlights do not include all the information needed to use NUWIQ safely and effectively. See full prescribing information for NUWIQ.
NUWIQ®, Antihemophilic Factor (Recombinant)
Lyophilized Powder for Solution for Intravenous Injection
Initial U.S. Approval: 2015

RECENT MAJOR CHANGES

Indications and Usage (1) 12/2024

Dosage and Administration, Dose (2.1) 12/2024

1 INDICATIONS AND USAGE

NUWIQ is a recombinant antihemophilic factor [blood coagulation factor VIII (Factor VIII)] indicated in pediatric and adult patients with Hemophilia A for (1):

On-demand treatment and control of bleeding episodes

Perioperative management of bleeding

Routine prophylaxis to reduce the frequency of bleeding episodes

NUWIQ is not indicated for the treatment of von Willebrand disease. (1)

2 DOSAGE AND ADMINISTRATION

For intravenous use after reconstitution

Each vial of NUWIQ is labeled with the actual amount of Factor VIII potency in international units (IU). (2.1)

Determine dose using the following formula for adolescents and adults (2.1):

Required IU = body weight (kg) x desired Factor VIII rise (%) (IU/dL) x 0.5 (IU/kg per IU/dL)

Dose and duration of therapy depends on severity of the FVIII deficiency, the location and extent of bleeding, FVIII level, and patient’s clinical condition. (2.1)

Dosing for routine prophylaxis: (2.1)

Patients | Dose (IU/kg) | Frequency of infusions
Adults and adolescents 12 - 17 yrs | 30 - 40 | Every other day
Children 2 - 11 yrs | 30 - 50 | Every other day or three times per week
Children < 2 yrs | 20 - 50 | Once per week to every other day

3 DOSAGE FORMS AND STRENGTHS

NUWIQ is available as a white sterile, non-pyrogenic, lyophilized powder for reconstitution in single-dose vials containing nominally 250, 500, 1000, 1500, 2000, 2500, 3000 or 4000 IU Factor VIII potency. (3)

4 CONTRAINDICATIONS

NUWIQ is contraindicated in patients who have manifested life-threatening hypersensitivity reactions, including anaphylaxis, to the product or its components (4)

5 WARNINGS AND PRECAUTIONS

Hypersensitivity reactions, including anaphylaxis, are possible. Should symptoms occur, discontinue NUWIQ and administer appropriate treatment. (5.1)

Development of Factor VIII neutralizing antibodies (inhibitors) may occur. If expected plasma Factor VIII activity levels are not attained, or if bleeding is not controlled with an appropriate dose, perform an assay that measures Factor VIII inhibitor concentration. (5.2)

Monitor all patients for Factor VIII activity and development of Factor VIII inhibitor antibodies. (5.3)

6 ADVERSE REACTIONS

The most frequently occurring adverse reactions (>5%) in clinical trials were upper respiratory tract infection, headache, fever, cough, lower respiratory tract infection, rhinitis, chills, abdominal pain, arthralgia, anemia, and pharyngitis. (6)

To report SUSPECTED ADVERSE REACTIONS, contact Octapharma USA Inc. at 1- 866-766-4860 or FDA at 1-800-FDA-1088 or www.fda.gov/medwatch.

8 USE IN SPECIFIC POPULATIONS

Pediatric Use: Lower recovery, shorter half life and faster clearance in children aged ≤ 12 years. Higher doses and/or a more frequent dosing schedule for prophylactic treatment should be considered in pediatric patients aged < 5 years. (8.4).

FULL PRESCRIBING INFORMATION

1 INDICATIONS AND USAGE

NUWIQ is a recombinant antihemophilic factor [blood coagulation factor VIII (Factor VIII)] indicated in pediatric and adult patients with Hemophilia A for:

- On-demand treatment and control of bleeding episodes
- Perioperative management of bleeding
- Routine prophylaxis to reduce the frequency of bleeding episodes

NUWIQ is not indicated for the treatment of von Willebrand disease.

2 DOSAGE AND ADMINISTRATION

For intravenous use after reconstitution

2.1 Dose

- Each vial of NUWIQ is labeled with the actual Factor VIII potency expressed in international units (IU). One IU of Factor VIII activity is defined by the quantity of Factor VIII in one mL of normal human pooled plasma. Calculation of the required dose of Factor VIII is based on the empirical finding that 1 IU Factor VIII per kg body weight raises the plasma Factor VIII activity by approximately 2% of normal activity or 2 IU/dL when assessed using the one stage clotting assay. Use the following formulae to determine the required dose:

- Dose and duration of therapy depend on the severity of the Factor VIII deficiency, the location and extent of the bleeding, FVIII level, and the patient’s clinical condition.

On-demand Treatment and Control of Bleeding Episodes

A guide for dosing NUWIQ for the on-demand treatment and control of bleeding episodes is provided in Table 1 . Selected dosing regimen should maintain plasma Factor VIII activity levels at or above the plasma levels (in % of normal or in IU/dL) outlined in the table.

Table 1: Dosing for Treatment and Control of Bleeding Episodes

Type of Bleeding Episodes | Required peak post-infusion Factor VIII activity (% of normal or IU/dL) | Frequency of Dosing (hours) | Duration of Therapy (days)
Minor: Superficial muscle or soft tissue and oral bleeds | 20–40 | 12-24 | At least 1 day, until the bleeding episode is resolved.
Moderate to Major: Hemorrhage into muscles, into oral cavity, hemarthrosis, known trauma | 30–60 | 12-24 | For 3–4 days or more until bleeding episode is resolved.
Life-threatening: Intracranial, intra-abdominal, gastro-intestinal or intrathoracic bleeds, central nervous system bleeds, bleeding in retropharyngeal spaces or iliopsoas sheath, eyes/retina, fractures or head trauma | 60–100 | 8-24 | Until bleeding risk is resolved.

Perioperative Management

A guide for dosing NUWIQ during surgery (perioperative management) is provided in Table 2 . Dosing should aim at maintaining a plasma Factor VIII activity level at or above the plasma levels (in % of normal or in IU/dL) outlined in the table.

Table 2: Dosing for Perioperative Management

Type of Surgery | Required post-infusion Factor VIII activity (% of normal or IU/dL) | Frequency of Doses (hours) | Duration of Therapy (days)
Minor including tooth extraction | 30–60 (pre- and post-operative) | 24 | At least 1 day, until healing is achieved.
Major Intracranial, intra-abdominal, or joint-replacement therapy | 80–100 (pre- and post-operative) | 8-24 | Until adequate wound healing, then continue therapy for at least another 7 days to maintain a Factor VIII activity of 30% to 60% (IU/dL).

Routine Prophylaxis

A guide for dosing NUWIQ for routine prophylaxis to reduce the frequency of bleeding is provided in Table 3 . Exact dosing should be defined by the patient’s clinical status and response.

Table 3: Dosing for Routine Prophylaxis

Patients | Dose (IU/kg) | Frequency of infusions
Adults and adolescents 12 - 17 yrs | 30 - 40 | Every other day
Children 2 - 11 yrs | 30 - 50 | Every other day or three times per week
Children < 2 yrs | 20 - 50 | Once per week to every other day

A regimen may be further individually adjusted to less or more frequent dosing at the discretion of the treating physician.

2.2 Preparation and Reconstitution

NUWIQ package contents:

- single-dose vial of NUWIQ concentrate
- pre-filled syringe containing 2.5 mL Sterile Water for Injection
- vial adapter
- butterfly needle
- two alcohol swabs.

1. Always work on a clean surface and wash your hands before performing the procedure.
2. Allow the vial of NUWIQ and the pre-filled syringe to come to room temperature.
3. Remove the plastic flip-top cap from the NUWIQ vial to expose the rubber stopper. (Figure A).
4. Wipe the top of the vial with an alcohol swab and allow the rubber stopper of the vial to dry.
5. Peel back the paper cover from the vial adapter package revealing the adapter spike without removing the adapter from the package (Figure B).
6. With the concentrate vial on an even surface, insert the adapter spike into the rubber stopper. The adapter snaps to the vial when done (Figure C).
7. Peel back the paper cover from the pre-filled syringe package. Connect plunger rod attaching the threaded end of the plunger rod to the solvent syringe, turning clockwise until a slight resistance is felt (Figure D). Avoid contact with shaft.
8. Break off the tamper-proof plastic tip from the syringe by snapping the perforation of the cap. Do not touch the inside of the cap or the syringe tip (Figure E).
9. Remove the adapter packaging and connect the syringe to the vial adapter by turning clockwise until resistance is felt (Figure F).
10. Slowly inject all liquid from syringe into the concentrate vial (Figure G).
11. Without removing the syringe, dissolve the concentrate powder in the vial by gently moving or swirling a few times. DO NOT SHAKE. Wait until all the powder dissolves completely.
12. Inspect the final solution for particles. The solution should be clear, colorless, and free from visible particles. Do not use if solution is cloudy or has particulate matter.
13. Turn the vial and syringe upside down (still attached).
14. Slowly withdraw the solution into the syringe. Make sure that all liquid is transferred to the syringe (Figure H).
15. Detach the filled syringe from the vial adapter by turning counter clockwise.

Do not refrigerate the solution after reconstitution. Use the solution within 3 hours after reconstitution. If solution is not used within this time period, close the filled syringe with the tamper-proof plastic tip, and discard.

2.3 Administration

For intravenous use after reconstitution only

1. Inspect the reconstituted NUWIQ solution for visible particulate matter and discoloration prior to administration. Do not use if particulate matter or discoloration is observed.
2. Do not administer NUWIQ in the same tubing or container as other medications.
3. Clean the chosen injection site with an alcohol swab.
4. Attach the provided infusion set to the syringe. Insert the needle of the infusion set into the chosen vein.
5. Perform intravenous bolus infusion. The rate of administration should be determined by patient’s comfort level, at a maximum rate of 4 mL per minute.
6. After infusing NUWIQ, remove and properly discard the infusion set. After the infusion, remove the peel-off label containing the batch number from the factor concentrate vial and place it in the log book for record keeping.

3 DOSAGE FORMS AND STRENGTHS

NUWIQ is available as a white, sterile, non-pyrogenic, lyophilized powder for reconstitution in single-dose vials containing nominally 250, 500, 1000, 1500, 2000, 2500, 3000, or 4000 IU Factor VIII potency. The actual Factor VIII potency is labeled on each NUWIQ vial.

4 CONTRAINDICATIONS

NUWIQ is contraindicated in patients who have manifested life-threatening hypersensitivity reactions, including anaphylaxis, to the product or its components.

5 WARNINGS AND PRECAUTIONS

5.1 Hypersensitivity Reactions

Hypersensitivity reactions, including anaphylaxis, are possible with NUWIQ. Early signs of hypersensitivity reactions that can progress to anaphylaxis may include angioedema, chest tightness, dyspnea, wheezing, urticaria, or pruritus. Immediately discontinue administration and initiate appropriate treatment if hypersensitivity reactions occur.

5.2 Neutralizing Antibodies

The formation of neutralizing antibodies (inhibitors) to Factor VIII can occur following the administration of NUWIQ. Monitor all patients for the development of Factor VIII inhibitors by appropriate clinical observations and laboratory tests. If the plasma Factor VIII level fails to increase as expected, or if bleeding is not controlled after NUWIQ administration, suspect the presence of an inhibitor (neutralizing antibody) [see Warnings and Precautions (5.3) ] .

5.3 Monitoring and Laboratory Tests

- Monitor plasma Factor VIII activity by performing a validated test (e.g., one stage clotting assay), to confirm that adequate Factor VIII levels have been achieved and maintained [see Dosage and Administration (2.1) ] .
- Monitor for the development of Factor VIII inhibitors. Perform a Bethesda inhibitor assay if expected Factor VIII plasma levels are not attained, or if bleeding is not controlled with the expected dose of NUWIQ. Use Bethesda Units (BU) to report inhibitor levels.

6 ADVERSE REACTIONS

The most common adverse reactions (>5% of patients) reported in clinical trials were upper respiratory tract infection, headache, fever, cough, lower respiratory tract infection, rhinitis, chills, abdominal pain, arthralgia, anemia, and pharyngitis.

6.1 Clinical Trials Experience

Because clinical trials are conducted under widely varying conditions, adverse reaction rates observed in the clinical trials of a drug cannot be directly compared to the rate in the clinical trials of another drug and may not reflect the rates observed in practice.

The safety profile of NUWIQ was evaluated in seven prospective, open-label clinical studies in previously treated patients (PTPs - exposed to a Factor VIII containing product for ≥150 exposure days (EDs) in the case of adolescents and adults or ≥50 EDs in the case of patients below 12 years of age) with severe Hemophilia A (Factor VIII ≤ 1%). Patients who had a history of detectable Factor VIII inhibitor, severe liver or kidney disease, were not immune competent (CD4+ count <200/µL), or scheduled to receive immunomodulating drugs, were excluded.

Across all clinical studies, 190 patients were stratified, among them, 129 were adults, 3 were adolescents between 12 and 17 years old, and 58 were pediatric patients between 2 and 11 years old. A total of 182 (95.8%) patients were treated for at least 180 days. Collectively, patients received between 24,005 and 2.12 million IU (555 to 34,713 IU/kg) from 14 to 918 infusions over a period of 14 to 896 exposure days. An exposure day was defined as any day on which at least one infusion was started.

With a total of 43,264 infusions over 42,808 EDs, adverse reactions reported in at least 5 of the 190 patients (2.6%) were upper respiratory tract infection (22%), headache (11%), fever (10%), cough (9.5%), lower respiratory tract infection (8.4%), rhinitis (7.9%), chills (6.8%), abdominal pain (5.3%), arthralgia (5.3%), pharyngitis (5.3%), diarrhea (4.7%), varicella (4.2%), device-related problems (4.2%), back pain (3.7%), extremity pain (3.7%), toothache (3.2%), vomiting (3.2%), head injury (2.6%), injury (2.6%), rash (2.6%), tonsillitis (2.6%), and tooth abscess (2.6%). Notably, dizziness was reported in 4 patients (2.1%); dyspnea, insomnia, and malaise in 2 patients (1.1%) each; and injection site pain, injection site inflammation, benign renal neoplasm, deterioration in neurological function/behavior, and syncope in 1 patient (0.5%) each.

Considering only the pediatric cohort of 59 patients (ages 2-12 years at initial enrollment), 48 of whom continued participation in a long-term extension study, 26,311 infusions totalling 1,019,528 IU/kg NUWIQ were administered. The most commonly reported adverse reactions (>10% of the 59 patients) were upper respiratory tract infection (49%), lower respiratory tract infection (24%), cough (20%), fever (20%), rhinitis (19%), pharyngitis (19%), chills (15%), varicella (14%), headache (12%), abdominal pain (10%), and extremity pain (10%). Dizziness was reported in 2 patients (3.4%), while deterioration in neurological function/behavior, insomnia, and syncope were each reported in 1 patient (1.7%).

6.2 Immunogenicity

All clinical trial patients (N = 190) were monitored for neutralizing antibodies (inhibitors) to Factor VIII by the modified Bethesda assay using blood samples obtained prior to the first infusion of NUWIQ in all studies, at defined intervals (at ED 10 to 15, at three months, and every further three months) in five studies, and every three months in one study and at the completion visit in all studies. No patient developed neutralizing antibodies to Factor VIII.

Non-neutralizing anti-Factor VIII antibodies (without inhibitory activity as measured by the modified Bethesda assay) were reported in four of 135 patients tested, giving a rate of 3%. Three of four patients had pre-existing non-neutralizing antibodies prior to exposure with NUWIQ. The binding antibodies were transient in two of these three patients. In one patient who was tested negative at screening, the non-neutralizing antibody was measured once at study end.

In a clinical trial, which enrolled 110 previously untreated patients (age range 0-146 months, no previous treatment with FVIII concentrates or other blood products containing FVIII was allowed), 108 had evaluable data post-treatment with NUWIQ. The primary endpoint of the study, inhibitor formation, was realized in 28 of 105 patients (26.7%; 95% CI: 18.5-36.2) with at least one inhibitor analysis after ED1. Seventeen patients (16.2%; 95% CI: 9.7-24.7) developed high-titer inhibitors and 11 (10.5%; 95% CI: 5.3-18) developed low-titer inhibitors, 5 of whom had transient inhibitors. Of the 28 patients who developed an inhibitor, 25 did so with ≤20 EDs prior to detection. All inhibitors developed within 34 ED.

The detection of antibody formation is highly dependent on the sensitivity and specificity of the assay. Additionally, the observed incidence of antibody (including neutralizing antibody) positivity in an assay may be influenced by several factors including assay methodology, sample handling, timing of sample collection, concomitant medications, and underlying disease. For these reasons, comparison of the incidence of antibodies to NUWIQ with the incidence of antibodies to other products may be misleading.

8 USE IN SPECIFIC POPULATIONS

8.1 Pregnancy

Risk Summary

There are no data with NUWIQ use in pregnant women to inform a drug-associated risk. Animal reproduction studies have not been conducted with NUWIQ. It is not known whether NUWIQ can cause fetal harm when administered to a pregnant woman or can affect reproduction capacity. In the U.S. general population, the estimated background risk of major birth defect and miscarriage in clinically recognized pregnancies is 2-4% and 15-20%, respectively.

8.2 Lactation

Risk Summary

There is no information regarding the presence of NUWIQ in human milk, the effect on the breastfed infant, or the effects on milk production. The developmental and health benefits of breastfeeding should be considered along with the mother’s clinical need for NUWIQ and any potential adverse effects on the breastfed infant from NUWIQ or from the underlying maternal condition.

8.4 Pediatric Use

The safety and efficacy of NUWIQ were assessed in a study in 59 previously treated pediatric patients (58 patients 2 to 11 years old) who received at least one dose of NUWIQ for routine prophylaxis. The safety and efficacy in routine prophylaxis and on-demand treatment of bleeding episodes are comparable between children and adults [see Adverse Reactions (6.1) and Clinical Studies (14) ] . The pediatric pharmacokinetic data of NUWIQ were obtained in 29 children between 2 and 5 years of age and 30 children between 6 and ≤12 years of age. Half-life (T 1/2) and incremental in vivo recovery (IVR) are lower in children than in adults and systemic drug clearance is substantially higher in the pediatric age group 2 to 5 yrs compared to adults. IVR in pediatric patients aged <2 yrs is lower than in all other age groups [see Clinical Pharmacology (12.3) ] . Higher doses and/or a more frequent dosing schedule for prophylactic treatment should be considered in pediatric patients aged <5 yrs.

The safety and efficacy of NUWIQ were assessed in a study in 110 previously untreated pediatric patients (PUPs, age range 0-146 months). Of 110 PUPs, 108 had evaluable data and were investigated to determine the immunogenicity [see Adverse Reactions (6.2) ] of NUWIQ, the primary endpoint. Secondary endpoints were efficacy during prophylaxis, on-demand, and surgical prophylaxis and safety and tolerability [see Adverse Reactions (6.1) ] .

8.5 Geriatric Use

Clinical studies of NUWIQ did not include sufficient numbers of patients age 65 and over to provide conclusive evidence as to whether or not they respond differently than younger patients.

11 DESCRIPTION

NUWIQ, Antihemophilic Factor (Recombinant), is a sterile, non-pyrogenic, lyophilized powder for reconstitution for intravenous injection. The product is supplied in single-dose vials containing nominal Factor VIII potencies of 250, 500, 1000, 1500, 2000, 2500, 3000 or 4000 IU. When reconstituted with 2.5 mL of solvent (Sterile Water for Injection), the respective nominal concentrations are 100, 200, 400, 600, 800, 1000, 1200 or 1600 IU/mL. The reconstituted product contains the following excipients per mL: 18 mg sodium chloride, 5.4 mg sucrose, 5.4 mg L-arginine hydrochloride, 0.3 mg calcium chloride dihydrate, 1.2 mg poloxamer 188, and 1.2 mg sodium citrate dihydrate. The concentration of each of the excipients is the same for all potencies. NUWIQ contains no preservatives. Each vial of NUWIQ is labeled with the actual Factor VIII potency expressed in IU determined using one-stage clotting assay, using a reference material calibrated against a World Health Organization (WHO) International Standard for Factor VIII concentrates. One IU, as defined by the WHO standard for human Factor VIII concentrates, is approximately equal to the level of Factor VIII activity in 1 mL of fresh pooled, normal, human plasma. The mean specific activity of NUWIQ is 8124 IU/mg total protein.

B-domain deleted recombinant coagulation Factor VIII (BDD-rFVIII) is the active ingredient in NUWIQ. BDD-rFVIII is a recombinant glycoprotein (a heterodimer) with an approximate molecular mass of 170 kDa, comprising the Factor VIII domains A1-A2 (so-called heavy chain of ~90 kDa) and A3-C1-C2 (so-called light chain of ~80 kDa), whereas the B-domain, present in the full-length plasma-derived Factor VIII, has been deleted. The purified protein consists of 1440 amino acids. The amino acid sequence is comparable to the B-domain deleted form of human plasma Factor VIII (90 + 80 kDa).

BDD-rFVIII is produced by recombinant DNA technology in genetically modified human embryonic kidney (HEK) 293F cells with no animal or human derived materials added during the manufacturing process or to the final product. As NUWIQ is produced using a human cell-line, it contains post-translational modifications comparable to human plasma-derived Factor VIII and is devoid of Neu5Gc or α-1,3-Gal epitopes that may be present in products produced in animal cells. Furthermore, BDD-rFVIII is fully sulfated at Tyr1680. The active substance is concentrated and purified by a series of chromatography steps, which also includes two dedicated viral clearance steps: solvent/detergent (S/D) treatment for virus inactivation and 20 nm nanofiltration for removal of viruses.

12 CLINICAL PHARMACOLOGY

12.1 Mechanism of Action

NUWIQ temporarily replaces the missing clotting Factor VIII that is needed for effective hemostasis.

12.2 Pharmacodynamics

Hemophilia A is a bleeding disorder characterized by a deficiency of functional coagulation Factor VIII, resulting in a prolonged plasma clotting time as measured by the activated partial thromboplastin time (aPTT) assay. Treatment with NUWIQ normalizes the aPTT over the effective dosing period.

12.3 Pharmacokinetics

The pharmacokinetics (PK) of NUWIQ were evaluated in an open-label, multi-center clinical study of 22 (20 adults and 2 adolescents) previously treated patients (PTPs) with severe Hemophilia A. The PK parameters (Table 4) were based on plasma Factor VIII activity measured by the one-stage clotting assay after a single intravenous infusion of a 50 IU/kg dose.

The PK profile obtained after 6 months of repeated dosing was comparable with the PK profile obtained after the first dose.

Table 4: Pharmacokinetic Parameters of NUWIQ in 22 PTP Adults/Adolescents (Dose: 50 IU/kg)

PK Parameters | Mean ± SD
AUC (h·IU/mL) | 18.0 ± 5.6
AUC norm (h·IU/mL/(IU/kg)) | 0.4 ± 0.1
C maxnorm (IU/mL/(IU/kg)) | 0.022 ± 0.003
T 1/2 (h) | 17.1 ± 11.2*
IVR (%/IU/kg) | 2.1 ± 0.3
MRT (h) | 22.5 ± 14.2
CL (mL/h/kg) | 3.0 ± 1.0
V ss (mL/kg) | 59.8 ± 19.8

AUC = Area under the curve (Factor VIII:C); AUCnorm = AUC divided by the dose; Cmaxnorm = Maximal plasma concentration divided by the dose; CL = Clearance; Factor VIII:C = Factor VIII coagulation activity; IVR = Incremental in vivo recovery; MRT = Mean residence time; PK = Pharmacokinetics; SD = Standard deviation; T1/2 = Terminal half-life; Vss = Volume of distribution at steady state; *Median, lower/upper quartile: 13.7, 12.0/17.5

Pediatric Pharmacokinetics

PK of pediatric patients is presented in Table 5 for the age groups 2 to 5 years and 6 to 12 years. They were based on plasma Factor VIII activity measured by the one-stage clotting assay after a single intravenous infusion of 50 IU/kg dose. Compared to adults and adolescents, IVR and T 1/2 were lower and systemic drug clearance (based on per kg bodyweight) was substantially higher in children 2 to 5 yr of age.

IVR analysis after 3 and 6 months of prophylactic treatment yielded comparable results with the IVR after the first dose.

As in the adult population, similar PK values were obtained using the chromogenic and the one-stage assay. The values in Table 5 reflect those obtained using the one-stage assay.

Table 5: Pharmacokinetic Parameters of NUWIQ in 26 PTP Children Age 2 to 5 Years and 6 to 12 Years (Dose: 50 IU/kg)

PK Parameters | 2 to 5 years (N = 13) Mean ± SD | 6 to ≤12 years (N = 13) Mean ± SD
AUC (h·IU/mL) | 10.1 ± 4.6 | 11.8 ± 2.7
AUC norm (h·IU/mL/(IU/kg)) | 0.2 ± 0.1 | 0.3 ± 0.1
C maxnorm (IU/mL/(IU/kg)) | 0.016 ± 0.002 | 0.017 ± 0.004
T 1/2 (h) | 11.9 ± 5.4 * | 13.1 ± 2.6 #
IVR (%/IU/kg) | 1.6 ± 0.2 | 1.6 ± 0.4
MRT (h) | 15.1 ± 7.4 | 16.5 ± 2.9
CL (mL/h/kg) | 5.4 ± 2.3 | 4.1 ± 0.9
V ss (mL/kg) | 68.3 ± 10.4 | 66.1 ± 16.0

AUC = Area under the curve (Factor VIII:C); AUC norm = AUC divided by the dose; C maxnorm = Maximal plasma concentration divided by the dose; CL = Clearance;Factor VIII:C = Factor VIII coagulation activity; IVR = Incremental in vivo recovery; MRT = Mean residence time; PK = Pharmacokinetics; SD = Standard deviation; T 1/2 = Terminal half-life; V ss = Volume of distribution at steady state; * Median, lower/upper quartile: 10.1, 9.4/13.7; # Median, lower/upper quartile: 12.8, 11.2/15.9

In 39 PUPs children <2 years of age, a dose of 40 IU FVIII/kg BW was administered for recovery determinations. The mean IVR in children <2 years of age was 1.1 %/IU/kg, lower than in adults and adolescents (IVR 2.1 %/IU/kg) and children aged 2–11 years (IVR 1.6 %/IU/kg).

13 NONCLINICAL TOXICOLOGY

13.1 Carcinogenesis, Mutagenesis, Impairment of Fertility

Long-term studies in animals to evaluate the carcinogenic potential of NUWIQ or studies to determine the effects of NUWIQ on genotoxicity or fertility have not been performed.

13.2 Animal Toxicology and/or Pharmacology

Local tolerance assessment of NUWIQ in rabbits following single perivenous administration at dosage strengths up to 4000 IU did not result in adverse findings.

14 CLINICAL STUDIES

The efficacy of NUWIQ was evaluated in three multi-center, open-label, prospective clinical trials in PTPs with severe Hemophilia A. For routine prophylaxis, the efficacy of NUWIQ was evaluated in two multi-center studies, one in adult patients (n = 32) and one in pediatric patients (n = 59). For the treatment of bleeding episodes, efficacy was evaluated in one multi-center study in adolescents (n = 2) and adults (n = 20) who were treated on-demand only, and also in patients who experienced breakthrough bleeding episodes in the two prophylaxis studies. Across all studies, patients undergoing surgical procedures were evaluated for hemostatic efficacy during perioperative management.

On-demand Treatment and Control of Bleeding Episodes

A total of 1124 bleeding episodes in 69 patients (35 adults, 2 adolescents, and 32 children) were treated with NUWIQ. Response to each treatment was assessed by the patients using an ordinal scale of excellent (abrupt pain relief and/or unequivocal improvement in objective signs of bleeding within approximately 8 hours after a single infusion), good (definite pain relief and/or improvement in signs of bleeding within approximately 8–12 hours after an infusion requiring up to 2 infusions for complete resolution), moderate (probable or slight beneficial effect within approximately 12 hours after the first infusion requiring more than two infusions for complete resolution), or none (no improvement within 12 hours, or worsening of symptoms, requiring more than 2 infusions for complete resolution).

The majority of treated bleeding episodes (n = 986) was from the study where patients only received on-demand treatment. 642 (65%) bleeding episodes occurred spontaneously, 341 (35%) were traumatic, and 3 (0.3%) bleeding episodes were due to other causes. The mean dose per injection used to treat a bleeding episode was 32 IU/kg. Hemostatic efficacy in response to NUWIQ treatment was rated as excellent or good in 94% and as moderate in 6% of the bleeds.

In case of breakthrough bleeding episodes, the mean dose per injection used to treat a bleeding episode was 33.3 IU/kg in adults (n=15 with 30 bleeding episodes) and 45 IU/kg in pediatric patients (n=32 with 108 bleeding episodes). The median number of injections to treat a bleeding episode was 1. Hemostatic efficacy was excellent or good in 100% of bleeds in adults and 82% of bleeds in pediatric patients.

Perioperative Management of Bleeding

Across all studies, the efficacy of NUWIQ in surgical prophylaxis was assessed in a total of 60 surgical procedures in 36 patients; 32 procedures in 16 patients were classed as minor and 28 procedures in 23 patients were classed as major. NUWIQ pre-operative dosing ranged from 33 IU/kg to 90 IU/kg per infusion. The total number of infusions administered ranged from one to 19 for minor procedures and three to 76 for major procedures; three procedures required an injection of NUWIQ during surgery.

The efficacy of surgical prophylaxis was rated for each case by a surgeon and a hematologist, taking into account both the intra- and postoperative assessment. Hemostasis efficacy was rated at the end of the surgery by the surgeon and postoperatively by the surgeon and hematologist using ordinal scales as follows:

- Excellent: Intra-operative: intra-operative blood loss lower than or equal to the average expected blood loss for the type of procedure performed in a patient with normal hemostasis; Postoperative: No postoperative bleeding or oozing that was not due to complications of surgery. All postoperative bleeding (due to complications of surgery) was controlled with NUWIQ as anticipated for the type of procedure.
- Good: Intra-operative: intra-operative blood loss was higher than average expected blood loss but lower than or equal to the maximal expected blood loss for the type of procedure in a patient with normal hemostasis; Postoperative: No postoperative bleeding or oozing that was not due to complications of surgery. Control of postoperative bleeding due to complications of surgery required increased dosing with NUWIQ or additional infusions, not originally anticipated for the type of procedure.
- Moderate: Intra-operative: Intra-operative blood loss was higher than maximal expected blood loss for the type of procedure performed in a patient with normal hemostasis, but hemostasis was controlled. Postoperative: Some postoperative bleeding and oozing that was not due to complications of surgery; control of postoperative bleeding required increased dosing with NUWIQ or additional infusions, not originally anticipated for the type of procedure.
- None: Intra-operative: Hemostasis was uncontrolled necessitating a change in clotting factor replacement regimen. Postoperative: Extensive uncontrolled postoperative bleeding and oozing. Control of postoperative bleeding required use of an alternate FVIII concentrate.

Efficacy for 28 major surgeries was rated as excellent in 23 (82%) cases, good in 4 (14%) cases, and moderate in 1 (4%) case. The efficacy of all 30 rated minor surgeries was excellent.

Routine Prophylaxis and Bleeding Control

In the study evaluating the efficacy and safety of NUWIQ for routine prophylaxis in 32 adult patients (29 White, 3 Asian), the product was given every other day with a dose of 30-40 IU/kg for at least 6 months. In another study evaluating the safety, immunogenicity and hemostatic efficacy in 59 pediatric patients aged 2 to 12 years (all White, 29 were 2 to 5 years old, and 30 between 6 and 12 years), patients received NUWIQ prophylactically every other day or 3 times per week for at least 6 months. Clinical outcomes are summarized in Table 6 .

Table 6. Clinical Outcomes in Adult and Pediatric Patients

 | Adults (N=32) | Children (N=59)
Mean dose (± standard deviation) | 32.8 ± 2.8 IU/kg | 38.9 ± 7.2 IU/kg
Patients with 0 bleeding episodes | 16 (50.0%) | 20 (33.9%)
Patients with 1 bleeding episode | 11 (34.4%) | 14 (23.7%)
Patients with 2 bleeding episodes | - | 3 (5.1%)
Patients with ≥ 3 bleeding episodes | - | 22 (37.3%)
Patients with ≥5 bleeding episodes | 5 (15.6%)
Annualized bleeding rate (per patient) - spontaneous bleeds | 1.16 ± 2.57 (median 0, range 0-8.6) | 1.50 ± 3.32 (median 0, range 0-13.8)
Annualized bleeding rate (per patient) for all types of bleeds | 2.28 ± 3.73 (median 0.9, range 0-14.7) | 4.12 ± 5.22 (median 1.90, range 0-20.7)
Reduction in annualized bleeding rate compared to on-demand treatment in a different study* | 96% | 93%

Severity of bleeds (% of bleeds) in the adults were major 16 (36.4%), minor – 28 (63.6%), life threatening 0. Severity of bleeds in the children was moderate or major 64 (42.6%), minor 61 (56.5%), unknown 1 (0.9%), life threatening 0. * Based on a negative binomial model.

In a study of 59 previously treated pediatric patients ages 2-12 years, the children received a total of 5746 infusions. Of these infusions, 5316 (93%) were for prophylaxis, 216 (4%) for the treatment of bleeding episodes, 41 (0.7%) for peri-operative management and 173 (3%) for pharmacokinetic (PK) and recovery assessments.

Long-term treatment with routine prophylaxis was evaluated in an extension of the pediatric study in which 49 children (2-5 years [N=26] and 6-12 years [N=23]) who had completed the original pediatric study were treated with an additional 20,518 infusions of NUWIQ over a mean of an additional 29.4 months. Across both studies, a total of 26,289 infusions and 33,724,769 IU (990,927 IU/kg) were given. Of these infusions, 25,040 (95.2%) were for prophylaxis, 700 (2.7%) for treatment of bleeding episodes, 304 (1.2%) for peri-operative management, 247 (0.9%) for recovery assessments, and 189 (0.7%) for pharmacokinetic analyses. The median dose per prophylactic infusion was 37 IU/kg (range 12.8-124 IU/kg).

The mean annualized bleeding rate was 3.5 ± 4.4 (median 2.2, range 0.0 – 24.7). Eight of the 59 children (14%) had no bleeds.

16 HOW SUPPLIED/STORAGE AND HANDLING

How Supplied

- NUWIQ is supplied in packages comprising a single-dose vial containing nominally 250, 500, 1000 2000, 2500, 3000 or 4000 international units (IU) of Factor VIII potency, a pre-filled syringe with 2.5 mL solvent (Water for Injection), a vial adapter, a butterfly needle and two alcohol swabs. The actual amount of NUWIQ in IU is stated on each carton and vial.
- Components used in the packaging of NUWIQ are not made with natural rubber latex.

Color | Nominal strength | Container NDC | Carton NDC
pale blue | NUWIQ 250 IU | 68982-140-01 | 68982-139-01
pale pink | NUWIQ 500 IU | 68982-142-01 | 68982-141-01
green blue | NUWIQ 1000 IU | 68982-144-01 | 68982-143-01
purple | NUWIQ 1500 IU | 68982-154-01 | 68982-153-01
orange | NUWIQ 2000 IU | 68982-146-01 | 68982-145-01
brown | NUWIQ 2500 IU | 68982-148-01 | 68982-147-01
dark grey | NUWIQ 3000 IU | 68982-150-01 | 68982-149-01
dark green | NUWIQ 4000 IU | 68982-152-01 | 68982-151-01

Storage and Handling

- Store NUWIQ in the original package to protect the NUWIQ vials from light.
- Store NUWIQ in powder form at 2 – 8°C (35 – 46°F) for up to 24 months. Do not freeze.
- During the shelf life, the product may be kept at room temperature [up to 25°C (77°F)] for a single period not exceeding 3 months. After storage at room temperature, do not return the product to the refrigerator.
- Do not use after the expiration date.
- Keep the reconstituted solution at room temperature. Do not refrigerate after reconstitution. Use the reconstituted solution immediately or within 3 hours after reconstitution. Discard any remaining solution.

17 PATIENT COUNSELING INFORMATION

- Advise patients to read the FDA-approved patient labeling (Patient Information and Instructions for Use)
- Because hypersensitivity reactions are possible with NUWIQ , inform patients of the early signs of hypersensitivity reactions, including hives, generalized urticaria, tightness of the chest, wheezing, hypotension, and anaphylaxis. Advise patients to stop the injection if any of these symptoms arise and contact their physician, and seek prompt emergency treatment.
- Advise patients to contact their physician or treatment center for further treatment and/or assessment if they experience a lack of clinical response to Factor VIII replacement therapy, as this may be a manifestation of an inhibitor.
- Advise patients to consult with their healthcare provider prior to traveling. While traveling, patients should be advised to bring an adequate supply of NUWIQ based on their current treatment regimen.

Manufactured by:

Octapharma AB

Lars Forssells gata 23

SE-112 75, Sweden

U.S. License No. 1646

Distributed by:

Octapharma USA, Inc.

117 West Century Road

Paramus, NJ 07652

PATIENT PACKAGE INSERT

FDA-APPROVED PATIENT LABELING

Patient Information

NUWIQ /nu’ veek /

Antihemophilic Factor (Recombinant)

Please read this Patient Information carefully before using NUWIQ and each time you get a refill, as there may be new information. This Patient Information does not take the place of talking with your healthcare provider about your medical condition or your treatment.

What is NUWIQ ?

NUWIQ is an injectable medicine that is used to help treat and control bleeding in adults and children with Hemophilia A (congenital clotting Factor VIII deficiency). NUWIQ can reduce the number of bleeding episodes in children and adults when used regularly (prophylaxis). Usually, Hemophilia A treatment is life-long.

Your healthcare provider may also give you NUWIQ when you have surgery.

NUWIQ is NOT used to treat von Willebrand disease.

Who should not use NUWIQ ?

You should not use NUWIQ if you had an allergic reaction to it in the past.

Tell your healthcare provider if you are (or are planning to become) pregnant and/or breastfeeding because NUWIQ may not be right for you.

What should I tell my healthcare provider before using NUWIQ ?

Talk to your healthcare provider about any medical conditions that you have or have had, including if you have been told that you have inhibitors to Factor VIII, because NUWIQ may not work for you.

Tell your healthcare provider about all of the prescription and non-prescription medicines you take, including over-the-counter medicines, dietary supplements, and/or herbal medicines.

How should I use NUWIQ ?

You get NUWIQ as an infusion into your vein. NUWIQ is sold as a powder in a vial. The powder is mixed with sterile water supplied in a prefilled syringe. See instructions for reconstitution and injection of NUWIQ.

Your healthcare provider will instruct you on how to do reconstitutions and infusions on your own or with the help of a family member. Your healthcare provider may watch you give yourself the first dose of NUWIQ .

You must carefully follow your healthcare provider’s instructions regarding the dose and schedule for infusing NUWIQ so that your treatment will work optimally for you.

NUWIQ comes in different dosage strengths. The actual number of international units (IU) of Factor VIII in the vial will be printed on the label and box. Always check the actual number of IU of Factor VIII printed on the label to make sure you are using the strength prescribed by your healthcare provider..

Contact your healthcare provider right away if bleeding is not controlled after using NUWIQ .

Talk to your healthcare provider before travelling. Plan to bring enough NUWIQ for your treatment during this time.

Do not stop using NUWIQ without consulting with your healthcare provider.

What are the possible side-effects of NUWIQ ?

Allergic reactions may occur with NUWIQ. Stop the injection immediately and call your healthcare provider or emergency department right away if you have any of the following symptoms: dizziness, loss of consciousness, difficulty breathing, wheezing, chest tightness, swelling of lips and tongue, rash, or hives.

Your body can also make antibodies (known as inhibitors) against Factor VIII, which may stop NUWIQ from working properly. Your healthcare provider may test your blood to check for inhibitors at regular intervals.

Side-effects that have been reported with NUWIQ include: injection site inflammation, injection site pain, prickling or tingling sensation, headache, back pain, dizziness, and dry mouth.

These are not all the possible side effects of NUWIQ. Talk to your healthcare provider about any side-effect that bothers you or that does not go away.

How should I store NUWIQ ?

Keep NUWIQ in its original box to protect it from exposure to light. Do not freeze NUWIQ .

You can store NUWIQ in the refrigerator for up to 24 months at 2-8°C (36-46°F). NUWIQ can be kept at room temperature [up to 25°C (77°F)] for a single period not exceeding 3 months (note on the carton the date when the product was removed from the refrigerator). After storage at room temperature, the product must be used or discarded, and it must not be put back into the refrigerator.

Do not use NUWIQ after the expiration date printed on the vial.

Do not use NUWIQ if the reconstituted solution is cloudy, contains particles, and/or is not colorless.

NUWIQ should be used as soon as possible after reconstitution. Protect reconstituted NUWIQ from light and temperatures above 25°C (77°F). Discard any product not used within three hours.

Dispose of all materials, including any unused NUWIQ , in an appropriate container.

What else should I know about NUWIQ ?

Do not use NUWIQ for a medical condition for which it was not prescribed. Do not share NUWIQ with other people, even if they have the same diagnosis and symptoms that you have.

Resources at Octapharma available to patients

For more product information on NUWIQ , please visit www.NUWIQ.com.

For more information on patient assistance programs that are available to you, please contact the Octapharma Patient Support Center at 1-800-554-4440.

For more information on additional Octapharma patient resources, please visit www.NUWIQ.com.

Manufactured by:

Octapharma AB

Lars Forssells gata 23

SE-112 75, Sweden

U.S. License No. 1646

Distributed by:

Octapharma USA, Inc.

117 West Century Road

Paramus, NJ 07652

NUWIQ is a registered trademark of Octapharma.

INSTRUCTIONS FOR USE

NUWIQ /nu’ veek /

Antihemophilic Factor (Recombinant)

Read these instructions carefully before using NUWIQ for the first time. You should ensure that you have the appropriate training from your healthcare provider or hemophilia treatment center before attempting a self-infusion of NUWIQ. Always follow the prescribed dose and specific instructions given by your healthcare provider. The general guidelines for mixing and infusing NUWIQ are listed below. If you are unsure of any of these steps, please contact your healthcare provider before using NUWIQ.

Instruction for Mixing NUWIQ

1. Always work on a clean surface and wash your hands before performing the procedure.
2. Allow the vial of NUWIQ and the pre-filled syringe to come to room temperature.
3. Remove the plastic flip-top cap from the NUWIQ vial to expose the rubber stopper (Figure A).
4. Wipe the top of the vial with an alcohol swab and allow the rubber stopper of the vial to dry.
5. Peel back the paper cover from the vial adapter package revealing the adapter spike without removing the adapter from the package (Figure B).
6. With the vial on an even surface, insert the adapter spike into the rubber stopper. The adapter snaps to the vial when done (Figure C).
7. Peel back the paper cover from the pre-filled syringe package. Connect plunger rod attaching the threaded end of the plunger rod to the solvent syringe, turning clockwise until a slight resistance is felt (Figure D). Avoid contact with the shaft of the plunger rod.
8. Break off the tamper-proof plastic tip from the syringe by snapping the perforation of the cap. Do not touch the inside of the cap or the syringe tip (Figure E).
9. Remove the adapter packaging and connect the syringe to the vial adapter by turning clockwise until resistance is felt (Figure F).
10. Slowly inject all liquid from syringe into the concentrate vial (Figure G).
11. Without removing the syringe, dissolve the concentrate powder in the vial by gently moving or swirling a few times. DO NOT SHAKE. Wait until all the powder dissolves completely.
12. Inspect the final solution for particles. The solution should be clear, colorless, and free from visible particles. Do not use if solution is cloudy or if it has visible particles.
13. Turn the vial and syringe upside down (still attached).
14. Slowly withdraw the solution into the syringe. Make sure that all liquid is transferred to the syringe (Figure H).
15. Detach the filled syringe from the vial adapter by turning counter clockwise.
16. Do not refrigerate the solution after reconstitution. Use the solution within 3 hours after reconstitution. If solution is not used within this time period, close the filled syringe with the tamper-proof plastic tip and discard the syringe.

Instructions for Injecting NUWIQ

For intravenous use after reconstitution only.

1. Inspect the reconstituted NUWIQ solution for visible particulate matter and discoloration prior to administration. Do not use if particles and/or discoloration are observed.
2. Do not administer NUWIQ in the same tubing or container as other medications.
3. Clean the chosen injection site with an alcohol swab.
4. Attach the provided infusion set to the syringe. Insert the needle of the infusion set into the chosen vein.
5. Perform intravenous bolus infusion. The rate of administration should be determined by the patient’s comfort level, at a maximum rate of 4 mL per minute.
6. After infusing NUWIQ, remove and properly discard the infusion set. After the infusion, remove the peel-off label containing the batch number from the factor concentrate vial and place it in the log book for record keeping. Discard the empty vial.

Manufactured by:

Octapharma AB

Lars Forssells gata 23

SE-112 75, Sweden

U.S. License No. 1646

Distributed by:

Octapharma USA, Inc.

117 West Century Road

Paramus, NJ 07652

NUWIQ is a registered trademark of Octapharma.

Issued September 2020.

PACKAGE LABEL - PRINCIPAL DISPLAY PANEL

Carton Label – Principal Display Panel

250 IU Range

NDC 68982-139-01

NUWIQ ®

Antihemophilic Factor (Recombinant)

Lyophilized Powder for Solution for Intravenous Injection

Manufactured by:

Octapharma AB

Lars Forssells gata 23

SE-112 75, Sweden

U.S. License No. 1646

Carton Label – Principal Display Panel

500 IU Range

NDC 68982-141-01

NUWIQ ®

Antihemophilic Factor (Recombinant)

Lyophilized Powder for Solution for Intravenous Injection

Manufactured by:

Octapharma AB

Lars Forssells gata 23

SE-112 75, Sweden

U.S. License No. 1646

Carton Label – Principal Display Panel

1000 IU Range

NDC 68982-143-01

NUWIQ ®

Antihemophilic Factor (Recombinant)

Lyophilized Powder for Solution for Intravenous Injection

Manufactured by:

Octapharma AB

Lars Forssells gata 23

SE-112 75, Sweden

U.S. License No. 1646

Carton Label – Principal Display Panel

1500 IU Range

NDC 68982-153-01

NUWIQ ®

Antihemophilic Factor (Recombinant)

Lyophilized Powder for Solution for Intravenous Injection

Manufactured by:

Octapharma AB

Lars Forssells gata 23

SE-112 75, Sweden

U.S. License No. 1646

Carton Label – Principal Display Panel

2000 IU Range

NDC 68982-145-01

NUWIQ ®

Antihemophilic Factor (Recombinant)

Lyophilized Powder for Solution for Intravenous Injection

Manufactured by:

Octapharma AB

Lars Forssells gata 23

SE-112 75, Sweden

U.S. License No. 1646

Carton Label – Principal Display Panel

2500 IU Range

NDC 68982-147-01

NUWIQ ®

Antihemophilic Factor (Recombinant)

Lyophilized Powder for Solution for Intravenous Injection

Manufactured by:

Octapharma AB

Lars Forssells gata 23

SE-112 75, Sweden

U.S. License No. 1646

Carton Label – Principal Display Panel

3000 IU Range

NDC 68982-149-01

NUWIQ ®

Antihemophilic Factor (Recombinant)

Lyophilized Powder for Solution for Intravenous Injection

Manufactured by:

Octapharma AB

Lars Forssells gata 23

SE-112 75, Sweden

U.S. License No. 1646

Carton Label – Principal Display Panel

4000 IU Range

NDC 68982-151-01

NUWIQ ®

Antihemophilic Factor (Recombinant)

Lyophilized Powder for Solution for Intravenous Injection

Manufactured by:

Octapharma AB

Lars Forssells gata 23

SE-112 75, Sweden

U.S. License No. 1646